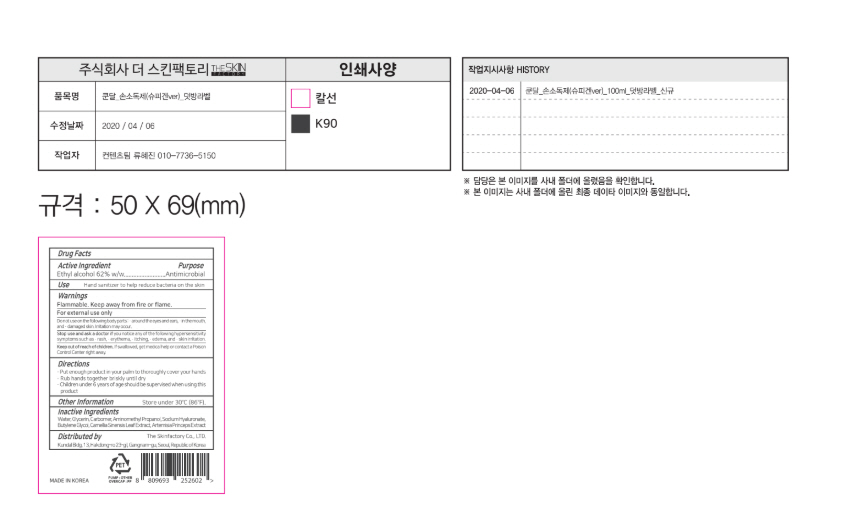 DRUG LABEL: Pure Green Hand Sanitizer Plus
NDC: 74773-0004 | Form: GEL
Manufacturer: THESKINFACTORY CO., LTD.
Category: otc | Type: HUMAN OTC DRUG LABEL
Date: 20200409

ACTIVE INGREDIENTS: ALCOHOL 62 g/100 mL
INACTIVE INGREDIENTS: BUTYLENE GLYCOL; WATER; GLYCERIN

Drug Facts

ACTIVE INGREDIENT

Alcohol

INACTIVE INGREDIENT

Water, Glycerin, Carbomer, Butylene Glycol, etc.

PURPOSE

Antimicrobial

KEEP OUT OF REACH OF THE CHILDREN

INDICATIONS AND USAGE

Store under 30°C (86°F)

WARNINGS

For external use only.

Flammable, keep away from fire or flame.

When using this product keep out of eyes. If contact with eyes occurs, rinse promptly and thoroughly with water.

Stop use and ask a doctor if significant irritation or sensitization develops.

Keep out of reach of children. If swallowed, get medical help or contact a Poison Control Center right away.

DOSAGE AND ADMINISTRATION

- Put enough product in your palm to thoroughly cover your hands
- Rub hands together briskly until dry
- Children under 6 years of age should be supervised when using this product